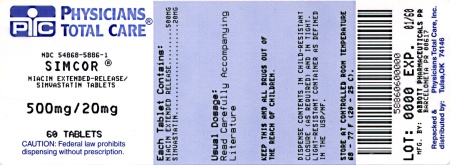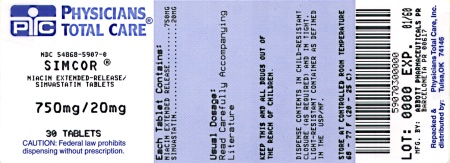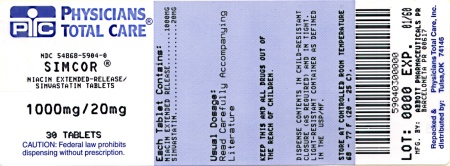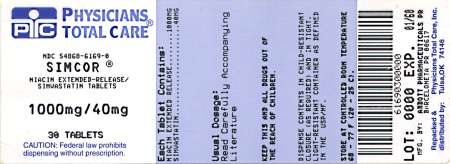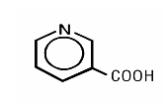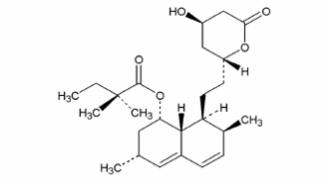 DRUG LABEL: Simcor
NDC: 54868-5886 | Form: TABLET, FILM COATED, EXTENDED RELEASE
Manufacturer: Physicians Total Care, Inc.
Category: prescription | Type: HUMAN PRESCRIPTION DRUG LABEL
Date: 20100806

ACTIVE INGREDIENTS: SIMVASTATIN 20 mg/1 1; NIACIN 500 mg/1 1
INACTIVE INGREDIENTS: HYPROMELLOSE; POVIDONE; STEARIC ACID; POLYETHYLENE GLYCOL; BUTYLATED HYDROXYANISOLE; FERROSOFERRIC OXIDE; FD&C BLUE NO. 2; LACTOSE MONOHYDRATE; TITANIUM DIOXIDE; TRIACETIN

HIGHLIGHTS OF PRESCRIBING INFORMATION

These highlights do not include all the information needed to use SIMCOR® safely and effectively. See full prescribing information for SIMCOR.
SIMCOR (simvastatin/niacin extended-release) tablet, film coated, extended release for oral use.
Initial U.S. Approval: 2008

1 INDICATIONS AND USAGE

SIMCOR is a combination of simvastatin, an HMG-Co-A reductase inhibitor, and niacin extended-release (NIASPAN), nicotinic acid. SIMCOR is indicated to:

- Reduce elevated total–C, LDL-C, Apo B, non-HDL-C, TG, or to increase HDL-C in patients with primary hypercholesterolemia and mixed dyslipidemia when treatment with simvastatin monotherapy or niacin extended-release monotherapy is considered inadequate. (1.1)
- Reduce TG in patients with hypertriglyceridemia when treatment with simvastatin monotherapy or niacin extended-release monotherapy is considered inadequate. (1.1)

Limitations of use:
No incremental benefit of SIMCOR on cardiovascular morbidity and mortality over and above that demonstrated for simvastatin monotherapy and niacin monotherapy has been established. (1.1)

2 DOSAGE AND ADMINISTRATION

- SIMCOR should be taken at bedtime with a low-fat snack. (2)
- Dose range: 500/20 mg to 2000/40 mg once daily. (2)
- Initial dose for patients naïve to or switching from immediate-release niacin: 500/20 mg once daily. (2)
- The initial dose for patients already receiving niacin extended-release should not exceed 2000/40 mg once daily. (2)
- Maintenance dose: 1000/20 mg to 2000/40 mg once daily. (2)
- Doses greater than 2000/40 mg daily are not recommended. (2)

3 DOSAGE FORMS AND STRENGTHS

- Unscored film-coated tablets:
  500 mg niacin extended-release/20 mg simvastatin (3)
  500 mg niacin extended-release/40 mg simvastatin (3)
  750 mg niacin extended-release/20 mg simvastatin (3)
  1000 mg niacin extended-release/20 mg simvastatin (3)
  1000 mg niacin extended-release/40 mg simvastatin (3)

4 CONTRAINDICATIONS

- Active liver disease, which may include unexplained persistent elevations in hepatic transaminase levels (4, 5.2)
- Active peptic ulcer disease (4)
- Arterial bleeding (4)
- Women who are pregnant or may become pregnant (4, 8.1)
- Nursing mothers (4, 8.3)
- Known hypersensitivity to product components (4, 6.1)

5 WARNINGS AND PRECAUTIONS

- Skeletal muscle effects (e.g., myopathy and rhabdomyolysis): Risks increase with higher doses, advanced age (≥ 65), hypothyroidism, renal impairment, and concomitant use of cyclosporine, danazol, gemfibrozil, amiodarone, and verapamil and potent CYP3A4 inhibitors. (5.1)
- Liver enzyme abnormalities and monitoring: Persistent elevations in hepatic transaminase can occur. Monitor liver enzymes before and during treatment. (5.2)
- Severe hepatic toxicity has occurred in patients substituting sustained-release niacin for immediate-release niacin at equivalent doses. If switching from niacin preparations other than niacin extended-release (NIASPAN), initiate with lowest SIMCOR dose; niacin extended-release can be converted at equivalent doses. (5.2)
- Niacin extended-release can increase serum glucose levels. Glucose levels should be closely monitored in diabetic or potentially diabetic patients particularly during the first few months of use. (5.3)

6 ADVERSE REACTIONS

The most common (incidence > 3%) adverse reactions with SIMCOR are flushing, headache, back pain, diarrhea, nausea, and pruritis. (6.1)

To report SUSPECTED ADVERSE REACTIONS, contact Abbott Laboratories at 1-800-633–9110 or FDA at 1-800-FDA-1088 or www.fda.gov/medwatch.

7 DRUG INTERACTIONS

- Potent inhibitors of CYP 3A4: Combination increases simvastatin exposure. SIMCOR should not be used with potent inhibitors of CYP3A4. (7.1)
- Cyclosporine: Combination with SIMCOR should be avoided. (7.2)
- Danazol: Combination with SIMCOR should be avoided. (7.2)
- Amiodarone: Combination with SIMCOR should be limited to the 20 mg once daily dose of simvastatin. (7.3)
- Verapamil: Combination with SIMCOR should be limited to the 20 mg once daily dose of simvastatin. (7.3)
- Gemfibrozil: Combination with SIMCOR should be avoided. (7.4)
- Fenofibrate: Combination with SIMCOR should be avoided. (7.4)
- Coumarin anticoagulants: Combination prolongs INR. Achieve stable INR prior to starting SIMCOR. Monitor INR frequently until stable upon initiation or alteration of SIMCOR therapy. (7.7)

8 USE IN SPECIFIC POPULATIONS

- Severe renal impairment (not on dialysis): SIMCOR should be used with extreme caution. (8.7)

FULL PRESCRIBING INFORMATION

1 INDICATIONS AND USAGE

Therapy with lipid-altering agents should be only one component of multiple risk factor intervention in individuals at significantly increased risk for atherosclerotic vascular disease due to hypercholesterolemia. Drug therapy is indicated as an adjunct to diet when the response to a diet restricted in saturated fat and cholesterol and other nonpharmacologic measures alone has been inadequate.

1.1 Patients with Hypercholesterolemia Requiring Modifications of Lipid Profiles

SIMCOR

SIMCOR is indicated to reduce total-C, LDL-C, Apo B, non-HDL-C, TG, or to increase HDL-C in patients with primary hypercholesterolemia and mixed dyslipidemia when treatment with simvastatin monotherapy or niacin extended-release monotherapy is considered inadequate.

SIMCOR is indicated to reduce TG in patients with hypertriglyceridemia when treatment with simvastatin monotherapy or niacin extended-release monotherapy is considered inadequate.

Limitations of use

No incremental benefit of SIMCOR on cardiovascular morbidity and mortality over and above that demonstrated for simvastatin monotherapy and niacin monotherapy has been established.

2 DOSAGE AND ADMINISTRATION

SIMCOR should be taken as a single daily dose at bedtime, with a low fat snack. Patients not currently on niacin extended-release and patients currently on niacin products other than niacin extended-release should start SIMCOR at a single 500/20 mg tablet daily at bedtime. Patients already taking simvastatin 20-40 mg who need additional management of their lipid levels may be started on a SIMCOR dose of 500/40 mg once daily at bedtime. [See Warnings and Precautions (5.2)]. The dose of niacin extended-release should not be increased by more than 500 mg daily every 4 weeks - see Table 1. The recommended maintenance dose for SIMCOR is 1000/20 mg to 2000/40 mg (two 1000/20 mg tablets) once daily depending on patient tolerability and lipid levels. The efficacy and safety of doses of SIMCOR greater than 2000/40 mg daily have not been studied and are therefore not recommended. If SIMCOR therapy is discontinued for an extended period of time (> 7 days), re-titration as tolerated is recommended. SIMCOR tablets should be taken whole and should not be broken, crushed, or chewed before swallowing.

Table 1. Recommended niacin extended-release dosing
 | Week(s) | Daily dose of niacin extended-release
Initial Titration Schedule | 1 to 4 | 500 mg
 | 5 to 8 | 1000 mg
 | * | 1500 mg
 | * | 2000 mg
* After Week 8, titrate to patient response and tolerance. If response to 1000 mg daily is inadequate, increase dose to 1500 mg daily; may subsequently increase dose to 2000 mg daily. Daily dose should not be increased more than 500 mg in a 4-week period, and doses above 2000 mg daily are not recommended.

Due to the increased risk of hepatotoxicity with other modified-release (sustained-release or time-release) niacin preparations or immediate-release (crystalline) niacin, SIMCOR should only be substituted for equivalent doses of niacin extended-release (NIASPAN).

Flushing [See Adverse Reactions (6.1)] may be reduced in frequency or severity by pretreatment with aspirin up to the recommended dose of 325 mg (taken approximately 30 minutes prior to SIMCOR dose). Flushing, pruritus, and gastrointestinal distress are also reduced by gradually increasing the dose of niacin (refer to Table 1) and avoiding administration on an empty stomach. Concomitant alcoholic, hot drinks or spicy foods may increase the side effects of flushing and pruritus and should be avoided around the time of SIMCOR ingestion.

3 DOSAGE FORMS AND STRENGTHS

SIMCOR tablets are formulated for oral administration in the following strength combinations:

Table 2. SIMCOR Tablet Strengths
 | 500mg/20mg | 500mg/40mg | 750mg/20mg | 1000mg/20mg | 1000mg/40mg
Niacin extended-release equivalent (mg) | 500 | 500 | 750 | 1000 | 1000
simvastatin equivalent (mg) | 20 | 40 | 20 | 20 | 40

4 CONTRAINDICATIONS

SIMCOR is contraindicated in the following conditions:

- Active liver disease, which may include unexplained persistent elevations in hepatic transaminase levels [See Warnings and Precautions (5.2)]
- Patients with active peptic ulcer disease
- Patients with arterial bleeding
- Women who are pregnant or may become pregnant. SIMCOR may cause fetal harm when administered to a pregnant woman. Serum cholesterol and triglycerides increase during normal pregnancy, and cholesterol or cholesterol derivatives are essential for fetal development. Atherosclerosis is a chronic process and discontinuation of lipid-lowering drugs during pregnancy should have little impact on long-term outcomes of primary hypercholesterolemia therapy. There are no adequate and well-controlled studies of SIMCOR use during pregnancy; however in rare reports congenital anomalies were observed following intrauterine exposure to HMG-CoA reductase inhibitors. If SIMCOR is used during pregnancy or if the patient becomes pregnant while taking this drug, the patient should be apprised of the potential hazard to the fetus. [See Use In Specific Populations (8.1) ] In rat and rabbit animal reproduction studies, simvastatin revealed no evidence of teratogenicity. There are no animal reproductive studies conducted with niacin.
- Nursing mothers. SIMCOR contains simvastatin and nicotinic acid. Nicotinic acid is excreted into human milk and it is not known whether simvastatin is excreted into human milk; however a small amount of another drug in this class does pass into breast milk. Because of the potential for serious adverse reactions in nursing infants, women who require SIMCOR treatment should not breastfeed their infants. [See Use In Specific Populations (8.3)]
- Patients with a known hypersensitivity to any component of this product. Hypersensitivity reactions including one of more of the following adverse reactions have been reported for simvastatin and/or niacin extended-release: anaphylaxis, angioedema, urticaria, fever, dyspnea, tongue edema, larynx edema, face edema, peripheral edema, laryngismus, and flushing. [See Adverse Reactions (6.1)]

5 WARNINGS AND PRECAUTIONS

SIMCOR should not be substituted for equivalent doses of immediate-release (crystalline) niacin. For patients switching from immediate-release niacin to SIMCOR, therapy with SIMCOR should be initiated at 500/20 mg and appropriately titrated to the desired therapeutic response. Patients already taking simvastatin 20-40 mg who need additional management of their lipid levels may be started on a SIMCOR dose of 500/40 mg once daily at bedtime. Doses of SIMCOR greater than 2000/40 mg are not recommended.

5.1 Myopathy/Rhabdomyolysis

Simvastatin

Simvastatin, like other inhibitors of HMG-CoA reductase, occasionally causes myopathy manifested as muscle pain, tenderness or weakness with creatine kinase (CK) above ten times the upper limit of normal (ULN). Myopathy sometimes takes the form of rhabdomyolysis with or without acute renal failure secondary to myoglobinuria, and rare fatalities have occurred. The risk of myopathy is increased by high levels of HMG-CoA reductase inhibitory activity in plasma.

As with other HMG-CoA reductase inhibitors, the risk of myopathy/rhabdomyolysis is dose related. In a clinical trial database in which 41,050 patients were treated with simvastatin with 24,747 (approximately 60%) treated for at least 4 years, the incidence of myopathy was approximately 0.02%, 0.08%, and 0.53% at 20, 40, and 80 mg/day, respectively. In these trials, patients were carefully monitored and some interacting medicinal products were excluded.

Potent inhibitors of CYP3A4: The risk of myopathy appears to be increased by high levels of HMG-CoA reductase inhibitory activity in plasma. Simvastatin is metabolized by the cytochrome P450 isoform 3A4. Certain drugs which share this metabolic pathway can raise the plasma levels of simvastatin and may increase the risk of myopathy. These include cyclosporine, itraconazole, ketoconazole, and other antifungal azoles, the macrolide antibiotics erythromycin and clarithromycin, and the ketolide antibiotic telithromycin, HIV protease inhibitors, the antidepressant nefazodone, or large quantities of grapefruit juice (> 1 quart daily).

The risk of myopathy/rhabdomyolysis is increased by concomitant use of simvastatin and, therefore, SIMCOR with the following:

Potent inhibitors of cytochrome P-450 isoform, 3A4 (CYP 3A4):

Itraconazole, ketoconazole, and other antifungal azoles
Macrolide antibiotics erythromycin, clarithromycin, and telithromycin
HIV protease inhibitors
Antidepressant nefazodone
Grapefruit juice in large quantities (> 1 quart daily)

The use of SIMCOR concomitantly with these potent CYP3A4 inhibitors should be avoided. [See Drug Interactions (7.1)]

Cyclosporine or Danazol: Simvastatin dose should not exceed 10 mg daily in combination with cyclosporine or danazol. Therefore, the combined used of SIMCOR with cyclosporine or danazol should be avoided. [See Drug Interactions (7.2)]

Gemfibrozil: Simvastatin dose should not exceed 10 mg daily when concomitantly used with gemfibrozil. Therefore, the combined use of SIMCOR with gemfibrozil should be avoided. [See Drug Interactions (7.4)]

Other Fibrates: Combined use of SIMCOR with drugs that cause myopathy/rhabdomyolysis when given alone, such as fibrates, should be avoided. [See Drug Interactions (7.4)]

Amiodarone or Verapamil: The dose of the simvastatin component of SIMCOR should not exceed 20 mg in patients receiving amiodarone or verapamil concomitantly. The combined use of the simvastatin at doses higher than 20 mg daily with amiodarone or verapamil should be avoided unless the clinical benefit is likely to outweigh the increased risk of myopathy. [See Drug Interactions (7.3)]

SIMCOR

Myopathy and/or rhabdomyolysis have been reported when simvastatin is used in combination with lipid-altering doses (≥ 1 gram/day) of niacin. Physicians contemplating the use of SIMCOR, a combination of simvastatin and niacin extended-release (NIASPAN), should weigh the potential benefits and risks, and should carefully monitor for any signs and symptoms of muscle pain, tenderness, or weakness, particularly during the initial month of treatment or during any period of upward dosage titration of either drug. Periodic determination of serum creatine kinase (CK) determinations may be considered in such situations, but there is no assurance that such monitoring will prevent myopathy.

Patients starting therapy with SIMCOR should be advised of the risk of myopathy, and told to report promptly unexplained muscle pain, tenderness, or weakness. A CK level above 10 times ULN in a patient with unexplained muscle symptoms indicates myopathy. SIMCOR therapy should be discontinued if myopathy is diagnosed or suspected.

In patients with complicated medical histories predisposing to rhabdomyolysis, such as renal insufficiency, dose escalation requires caution. Also, as there are no known adverse consequences of brief interruption of therapy, treatment with SIMCOR should be stopped for a few days before elective major surgery and when any major acute medical or surgical condition supervenes (e.g., sepsis, hypotension, dehydration, major surgery, trauma, severe metabolic, endocrine, and electrolyte disorders, or uncontrolled seizures).

5.2 Liver Dysfunction

Cases of severe hepatic toxicity, including fulminant hepatic necrosis, have occurred in patients who have substituted sustained-release (modified-release, timed-release) niacin products for immediate-release (crystalline) niacin at equivalent doses. Patients previously receiving niacin products other than niacin extended-release (NIASPAN) should be started on SIMCOR at the lowest recommended starting dose. [See Dosage and Administration (2)]

SIMCOR should be used with caution in patients who consume substantial quantities of alcohol and/or have a past history of liver disease. Active liver disease or unexplained transaminase elevations are contraindications to the use of SIMCOR. [See Contraindications (4)]

Niacin extended-release (NIASPAN) and simvastatin can cause abnormal liver tests. In a simvastatin-controlled, 24 week study with SIMCOR in 641 patients, there were no persistent increases (to more than 3x the ULN) in serum transaminases. In three placebo-controlled clinical studies of niacin extended-release, patients with normal serum transaminases levels at baseline did not experience any transaminase elevations greater than 3x the ULN. Persistent increases (to more than 3x the ULN) in serum transaminases have occurred in approximately 1% of patients who received simvastatin in clinical studies. When drug treatment was interrupted or discontinued in these patients, the transaminases levels usually fell slowly to pretreatment levels. The increases were not associated with jaundice or other clinical signs or symptoms. There was no evidence of hypersensitivity.

Liver function tests should be performed on all patients during therapy with SIMCOR. It is recommended that liver function tests be performed before treatment begins, every 12 weeks for the first 6 months, and periodically thereafter (e.g., at approximately 6-month intervals). Patients who develop increased transaminase levels should be monitored with a second liver function evaluation to confirm the finding and be followed thereafter with frequent liver function tests until the abnormality returns to normal. Should an increase in transaminase levels of more than 3x ULN persist, or if transaminase elevations are associated with symptoms of nausea, fever, and/or malaise, withdrawal of SIMCOR therapy is recommended.

5.3 Laboratory Abnormalities

Increase in Blood Glucose: Niacin treatment can increase fasting blood glucose. In a simvastatin-controlled, 24-week study with SIMCOR the change from baseline in glycosylated hemoglobin levels was 0.2% for SIMCOR-treated patients and 0.2% for simvastatin-treated patients. Diabetic or potentially diabetic patients should be observed closely during treatment with SIMCOR, particularly during the first few months of therapy. Adjustment of diet and/or hypoglycemic therapy or discontinuation of SIMCOR may be necessary.

Reduction in platelet count: Niacin can reduce platelet count. In a simvastatin-controlled, 24-week study with SIMCOR the mean percent change from baseline for patients treated with 2000/40 mg daily was -5.6%.

Increase in ProthrombinTime (PT): Niacin can cause small increases in PT . In a simvastatin-controlled, 24-week study with SIMCOR this effect was not seen.

Increase in Uric Acid: Elevated uric acid levels have occurred with niacin therapy. In a simvastatin-controlled, 24-week study with SIMCOR this effect was not seen. Nevertheless, in patients predisposed to gout, SIMCOR therapy should be used with caution.

Decrease in Phosphorus: Small dose-related reductions in phosphorous levels were seen in clinical studies with niacin. In a simvastatin-controlled, 24-week study with SIMCOR this effect was not seen.

6 ADVERSE REACTIONS

Overview

In a controlled clinical study, 14% of patients randomized to SIMCOR discontinued therapy due to an adverse event. Flushing episodes (i.e., warmth, redness, itching and/or tingling) were the most common treatment-emergent adverse reactions, occurring in up to 59% of patients treated with SIMCOR. Spontaneous reports with niacin extended-release and clinical studies of SIMCOR suggest that flushing may be accompanied by symptoms of dizziness or syncope, tachycardia, palpitations, shortness of breath, sweating, burning sensation/skin burning sensation, chills, and/or edema.

6.1 Clinical Studies Experience

SIMCOR

Because clinical studies are conducted under widely varying conditions, adverse reaction rates observed in the clinical studies of a drug cannot be directly compared to rates in the clinical studies of another drug and may not reflect the rates observed in practice.

The safety data described below reflect exposure to SIMCOR in 403 patients in a controlled study for a period of 6 months.

Flushing: Flushing (warmth, redness, itching and/or tingling) occurred in up to 59% of patients treated with SIMCOR. Flushing resulted in study discontinuation for 6.0% of patients.

More Common Adverse Reactions: In addition to flushing, adverse reactions occurring in ≥ 3% of patients (irrespective of investigator causality) treated with SIMCOR are shown in Table 3 below:

Table 3. Adverse Reactions Occurring in ≥ 3% of Patients in a Controlled Clinical Trial
Adverse Event | SIMCOR overall * | Simvastatin overall **
Total Number of Patients | N=403 | N=238
Headache | 18 (4.5%) | 11 (4.6%)
Pruritus | 13 (3.2%) | 0 (0.0%)
Nausea | 13 (3.2%) | 10 (4.2%)
Back Pain | 13 (3.2%) | 5 (2.1%)
Diarrhea | 12 (3.0%) | 7 (2.9%)
* SIMCOR overall included all doses from 500/20 mg to 2000/40 mg
** Simvastatin overall included 20 mg, 40 mg, and 80 mg doses

Simvastatin

In pre-marketing controlled clinical studies and their open extensions (2,423 patients with mean duration of follow-up of approximately 18 months) 1.4% of patients discontinued due to adverse reactions. The most commonly reported adverse reactions (incidence > 1%) in simvastatin controlled clinical trials were: headache (3.5%), abdominal pain (3.5%), constipation (2.3%), upper respiratory infection (2.1%), diarrhea (1.9%), and flatulence (1.9%).

Niacin Extended-Release

In placebo-controlled clinical trials (n=245), flushing episodes were the most common treatment-emergent adverse events (up to 88% of patients) for niacin extended-release. Other adverse events occurring in 5% or greater of patients treated with niacin extended-release are headache (9%), diarrhea (7%), nausea (5%), rhinitis (5%), and dyspepsia (4%) at a maintenance dose of 1000mg daily.

Clinical Laboratory Abnormalities:

SIMCOR

Chemistry

Elevations in serum transaminases [See Warnings and Precautions (5.2)], CK, fasting glucose, uric acid, alkaline phosphatase, LDH, amylase, γ-glutamyl transpeptidase, bilirubin, and reductions in phosphorus, and abnormal thyroid function tests.

Hematology

Reductions in platelet counts and prolongation of PT. [See Warnings and Precautions (5.3)]

6.2 Postmarketing Experience

Because the below reactions are reported voluntarily from a population of uncertain size, it is generally not possible to reliably estimate their frequency or establish a causal relationship to drug exposure.

Simvastatin

The following additional adverse reactions have been identified during postapproval use of simvastatin. Hypersensitivity reaction including one or more of the following features: anaphylaxis, angioedema, lupus erythematous-like syndrome, vasculitis, purpura, thrombocytopenia, leucopenia, hemolytic anemia, positive ANA, ESR increase, eosinophilia, arthritis, photosensitivity, chills, toxic epidermal necrolysis, erythema multiforme, Stevens-Johnson syndrome, urticaria, fever, dyspnea, and arthralgia; pancreatitis, hepatitis, hepatic failure, pruritus, cataracts, polymyositis, dermatomyositis, polymyalgia rheumatica, global amnesia, tendon rupture, peripheral neuropathy, memory impairment.

NIASPAN

The following additional adverse reactions have been identified during post-approval use of NIASPAN. Hypersensitivity reaction including one or more of the following features: anaphylaxis, dyspnea, angioedema, tongue edema, larynx edema, face edema, laryngismus; tachycardia, atrial fibrillation, other cardiac arrhythmias, palpitations, hypotension, postural hypotension, dizziness, syncope, flushing, burning sensation/skin burning sensation, paresthesia, urticaria, vesiculobullous rash, maculopapular rash, sweating, dry skin, skin discoloration, blurred vision, macular edema, myalgia, myopathy, peptic ulcers, eructation, flatulence, hepatitis, jaundice, peripheral edema, asthenia, nervousness, insomnia, migraine, gout, and decreased glucose tolerance.

7 DRUG INTERACTIONS

No drug interaction studies were conducted with SIMCOR. However, the following interactions have been noted with the individual components of SIMCOR:

Simvastatin

7.1 CYP3A4 Inhibitors

Simvastatin, like several other inhibitors of HMG-CoA reductase, is a substrate of CYP3A4. Simvastatin is metabolized by CYP3A4 but has no CYP3A4 inhibitory activity; therefore it is not expected to affect the plasma concentrations of other drugs metabolized by CYP3A4.

Potent inhibitors of CYP3A4 include:

Itraconazole, ketoconazole, and other antifungal azoles,

Macrolide antibiotics erythromycin, clarithromycin, and telithromycin,

HIV protease inhibitors,

Antidepressant nefazodone,

Grapefruit juice in large quantities (> 1 quart daily).

Potent inhibitors of CYP3A4 increase the risk of myopathy by reducing the elimination of simvastatin. Hence when simvastatin is used with a potent inhibitor of CYP3A4, elevated plasma levels of HMG-CoA reductase inhibitory activity can increase the risk of myopathy and rhabdomyolysis, particularly with higher doses of simvastatin. [See Warnings and Precautions (5.1)]

Serious skeletal muscle disorder, e.g., rhabdomyolysis, have been reported during concomitant therapy of simvastatin or other HMG-CoA reductase inhibitors with cyclosporine, danazol, itraconazole, ketoconazole, gemfibrozil, niacin, erythromycin, clarithromycin, telithromycin, nefazodone or HIV protease inhibitors.

Concomitant use of drugs labeled as potent inhibitors of CYP3A4 should be avoided unless the benefits of combined therapy outweigh the increased risk. If treatment with itraconazole, ketoconazole, erythromycin, clarithromycin or telithromycin is unavoidable, therapy with SIMCOR should be suspended during the course of treatment.

7.2 Cyclosporine or Danazol

Although the mechanism is not fully understood, cyclosporine has been shown to increase the area under the curve (AUC) of HMG-CoA reductase inhibitors. The increase in AUC for simvastatin acid is presumably due, in part, to inhibition of CYP3A4. The risk of myopathy/rhabdomyolysis is increased by concomitant administration of cyclosporine or danazol particularly with higher doses of simvastatin. [See Warnings and Precautions (5.1)]

7.3 Amiodarone or Verapamil

The risk of myopathy/rhabdomyolysis is increased by concomitant administration of amiodarone or verapamil with higher doses of simvastatin. [See Warnings and Precautions (5.1)]

7.4 Gemfibrozil and other Fibrates

Coadministration of gemfibrozil (600 mg twice daily for 3 days) with simvastatin (40 mg daily) resulted in clinically significant increases in simvastatin acid AUC (185%) and peak plasma concentration (Cmax,112%), possibly due to inhibition of simvastatin acid glucuronidation by gemfibrozil. The increase in simvastatin exposure increases the risk of myopathy when coadministred with gemfibrozil. The combined use of SIMCOR with gemfibrozil should be avoided [See Warnings and Precautions (5.1)]. The risk of myopathy also increases to a lesser extent when simvastatin is used in combination with other fibrates. Coadministration of 160 mg fenofibrate daily with 80 mg simvastatin daily for 7 days had no effect on plasma AUC (and Cmax) of either total HMG-CoA reductase inhibitory activity or fenofibric acid; there was a modest reduction (approximately 35%) of simvastatin acid which was not considered clinically significant.

7.5 Propranolol

In healthy male volunteers there was a significant decrease in mean Cmax, but no change in AUC, for simvastatin total and active inhibitors with concomitant administration of single doses of simvastatin and propranolol. The clinical relevance of this finding is unclear. The pharmacokinetics of the enantiomers of propranolol were not affected.

7.6 Digoxin

Concomitant administration of a single dose of digoxin in healthy male volunteers receiving simvastatin resulted in a slight elevation (less than 0.3 ng/mL) in digoxin concentrations in plasma (as measured by a radioimmunoassay) compared to concomitant administration of placebo and digoxin. Patients taking digoxin should be monitored appropriately when SIMCOR is initiated.

7.7 Coumarin Anticoagulants

In normal volunteers and hypercholesterolemic patients, simvastatin 20-40 mg/day modestly potentiated the effect of coumarin anticoagulants since the prothrombin time, reported as International Normalized Ratio (INR), increased from a baseline of 1.7 to 1.8 and from 2.6 to 3.4 in the volunteers and patients, respectively. With other reductase inhibitors, clinically evident bleeding and/or increased prothrombin time has been reported in a few patients taking coumarin anticoagulants concomitantly. In such patients, prothrombin time should be determined before starting SIMCOR and frequently enough during early therapy to ensure that no significant alteration of prothrombin time occurs. Once a stable prothrombin time has been documented, prothrombin times can be monitored at the intervals usually recommended for patients on coumarin anticoagulants. If the dose of SIMCOR is changed or discontinued, the same procedure should be repeated.

Niacin

7.8 Aspirin

Concomitant use of aspirin may decrease the metabolic clearance of niacin. The clinical relevance of this finding is unclear.

7.9 Antihypertensive Therapy

Niacin may potentiate the effects of ganglionic blocking agents and vasoactive drugs resulting in postural hypotension.

7.10 Bile Acid Sequestrants

An in vitro study was carried out investigating the niacin-binding capacity of colestipol and cholestyramine. About 98% of available niacin was bound to colestipol, with 10 to 30% binding to cholestyramine. These results suggest that 4 to 6 hours, or as great an interval as possible, should elapse between the ingestion of bile acid-binding resins and the administration of SIMCOR.

7.11 Other

Nutritional supplements containing large doses of niacin or related compounds may potentiate the adverse effects of SIMCOR.

8 USE IN SPECIFIC POPULATIONS

8.1 Pregnancy

Pregnancy Category X – [See Contraindications (4)]

SIMCOR is contraindicated in women who are or may become pregnant. Lipid lowering drugs offer no benefit during pregnancy, because cholesterol and cholesterol derivatives are needed for normal fetal development. Serum cholesterol and triglycerides increase during normal pregnancy. Atherosclerosis is a chronic process, and discontinuation of lipid-lowering drugs during pregnancy should have little impact on long-term outcomes of primary hypercholesterolemia therapy. There are no adequate and well-controlled studies of SIMCOR use during pregnancy; however, there are rare reports of congenital anomalies in infants exposed to HMG-CoA reductase inhibitors in utero. Animal reproduction studies of simvastatin in rats and rabbits showed no evidence of teratogenicity. SIMCOR may cause fetal harm when administered to a pregnant woman. If SIMCOR is used during pregnancy or if the patient becomes pregnant while taking this drug, the patient should be apprised of the potential hazard to the fetus.

SIMCOR contains simvastatin (a HMG-CoA reductase inhibitor) and niacin (nicotinic acid). There are rare reports of congenital anomalies following intrauterine exposure to HMG-CoA reductase inhibitors. In a review of approximately 100 prospectively followed pregnancies in women exposed to simvastatin or another structurally related HMG-CoA reductase inhibitor, the incidences of congenital anomalies, spontaneous abortions, and fetal deaths/stillbirths did not exceed those expected in the general population. However, the study was only able to exclude a 3- to 4-fold increased risk of congenital anomalies over the background rate. In 89% of these cases, drug treatment was initiated prior to pregnancy and was discontinued during the first trimester when pregnancy was identified. It is not known whether niacin at doses used for lipid disorders can cause fetal harm when administered to a pregnant woman.

Simvastatin was not teratogenic in rats or rabbits at doses that resulted in 3 times the human exposure based on mg/m^2 surface area. However, in studies with another structurally-related HMG-CoA reductase inhibitor, skeletal malformations were observed in rats and mice. Animal reproduction studies have not been conducted with niacin.

Women of childbearing potential, who require SIMCOR treatment for a lipid disorder, should use effective contraception. Patients trying to conceive should contact their prescriber to discuss stopping SIMCOR treatment. If pregnancy occurs, SIMCOR should be immediately discontinued.

8.3 Nursing Mothers

It is not known whether simvastatin is excreted into human milk; however, a small amount of another drug in this class does pass into breast milk. Niacin is excreted into human milk but the actual infant dose or infant dose as a percent of the maternal dose is not known. Because of the potential for serious adverse reactions in nursing infants, nursing mothers who require SIMCOR treatment should not breastfeed their infants. A decision should be made whether to discontinue nursing or discontinue drug, taking into account the importance of the drug to the mother. [see Contraindications (4)].

8.4 Pediatric Use

The safety and effectiveness of SIMCOR in pediatric patients have not been established.

8.5 Geriatric Use

There were 281 (30.8%) patients aged 65 years and older treated with SIMCOR in Phase III clinical studies. No overall differences in safety and effectiveness were observed between these patients and younger patients, but greater sensitivity of some older individuals cannot be ruled out. A pharmacokinetic study with simvastatin showed the mean plasma level of HMG-CoA reductase inhibitory activity to be approximately 45% higher in elderly patients between 70-78 years of age compared with patients between 18-30 years of age.

8.6 Gender

Data from the clinical trials suggest that women have a greater hypolipidemic response than men at equivalent doses of niacin extended-release. No consistent gender differences in efficacy and safety were observed in SIMCOR studies.

8.7 Renal Impairment

No pharmacokinetic studies have been conducted in patients with renal impairment for SIMCOR. Caution should be exercised when SIMCOR is administered to patients with renal disease. For patients with severe renal insufficiency, SIMCOR should not be started unless the patient has already tolerated treatment with simvastatin at a dose of 10 mg or higher. Caution should be exercised when SIMCOR is administered to these patients and they should be closely monitored.

8.8 Hepatic Impairment

No pharmacokinetic studies have been conducted in patients with hepatic insufficiency for SIMCOR. [See Warnings and Precautions (5.2)]

10 OVERDOSAGE

Supportive measures should be taken in the event of an overdose. The dialyzability of niacin, or of simvastatin and its metabolites, is not known.

A few cases of overdosage with simvastatin have been reported; the maximum dose taken was 3.6 g. All patients recovered without sequelae.

11 DESCRIPTION

SIMCOR tablets contain niacin extended-release (NIASPAN) and simvastatin in combination. Simvastatin, an inhibitor of HMG-CoA reductase, and niacin are both lipid-altering agents.

Niacin Extended-Release

Niacin is nicotinic acid, or 3-pyridinecarboxylic acid. Niacin is a white, nonhygroscopic crystalline powder that is very soluble in water, boiling ethanol, and propylene glycol. It is insoluble in ethyl ether. The empirical formula of niacin is C6H5NO2 and its molecular weight is 123.11. Niacin has the following structural formula:

Simvastatin

Simvastatin is butanoic acid, 2,2-dimethyl-,1,2,3,7,8,8a-hexahydro-3-7-dimethyl-8-[2-(tetrahydro-4-hydroxy-6-oxo-2H-pyran-2-yl)-ethyl]-1-naphthalenyl ester, [1S-[1α,3α,7β,8β(2S*4S*),-8aβ]]. Simvastatin is a white to off-white, nonhygroscopic, crystalline powder that is practically insoluble in water and freely soluble in chloroform, methanol, and ethanol. The empirical formula of simvastatin is C25H38O5 and its molecular weight is 418.57. Simvastatin has the following structural formula:

SIMCOR is available for oral administration as tablets containing 500 mg of niacin extended-release (NIASPAN) and 20 mg simvastatin (SIMCOR 500/20 mg), 500 mg of niacin extended-release (NIASPAN) and 40 mg simvastatin (SIMCOR 500/40 mg), 750 mg of niacin extended-release (NIASPAN) and 20 mg simvastatin (SIMCOR 750/20 mg), 1000 mg of niacin extended-release (NIASPAN) and 20 mg simvastatin (SIMCOR 1000/20 mg) and 1000 mg of niacin extended-release (NIASPAN) and 40 mg simvastatin (SIMCOR 1000/40 mg). Each tablet contains the following inactive ingredients: hypromellose, povidone, stearic acid, polyethylene glycol, butylated hydroxyanisole, FD&C Blue #2, lactose monohydrate, titanium dioxide, triacetin. SIMCOR 500/20 mg, SIMCOR 750/20 mg, and SIMCOR 1000/20 mg also contain iron oxide.

12 CLINICAL PHARMACOLOGY

12.1 Mechanism of Action

Niacin

Niacin functions in the body after conversion to nicotinamide adenine dinucleotide (NAD) in the NAD coenzyme system. The mechanism by which niacin alters lipid profiles is not completely understood and may involve several actions, including partial inhibition of release of free fatty acids from adipose tissue, and increased lipoprotein lipase activity (which may increase the rate of chylomicron triglyceride removal from plasma). Niacin decreases the rate of hepatic synthesis of VLDL-C and LDL-C, and does not appear to affect fecal excretion of fats, sterols, or bile acids.

Simvastatin

Simvastatin is a prodrug and is hydrolyzed to its active ß-hydroxyacid form, simvastatin acid, after administration. Simvastatin is a specific inhibitor of 3-hydroxy-3-methylglutaryl-coenzyme A (HMG-CoA) reductase, the enzyme that catalyzes the conversion of HMG-CoA to mevalonate, an early and rate-limiting step in the biosynthetic pathway for cholesterol. In addition, simvastatin reduces VLDL and TG and increases HDL-C.

12.2 Pharmacodynamics

A variety of clinical studies have demonstrated that elevated levels of Total-C, LDL-C, and Apo B promote human atherosclerosis. Similarly, decreased levels of HDL-C are associated with the development of atherosclerosis. Epidemiological investigations have established that cardiovascular morbidity and mortality vary directly with the level of Total-C and LDL-C, and inversely with the level of HDL-C.

Like LDL, cholesterol-enriched triglyceride-rich lipoproteins, including VLDL, intermediate-density lipoprotein (IDL), and their remnants, can also promote atherosclerosis. Elevated plasma TG are frequently found in a triad with low HDL-C levels and small LDL particles, as well as in association with non-lipid metabolic risk factors for coronary heart disease (CHD). As such, total plasma TG has not consistently been shown to be an independent risk factor for CHD. Furthermore, the independent effect of raising HDL-C or lowering TG on the risk of coronary and cardiovascular morbidity and mortality has not been determined.

SIMCOR

SIMCOR reduces total-C, LDL-C, non-HDL-C, Apo B, TG, and Lp(a) levels and increases HDL-C in patients with primary hyperlipidemia, mixed dyslipidemia, or hypertriglyceridemia.

Niacin

Niacin (but not nicotinamide) in gram doses reduces LDL-C, Apo B, Lp(a), TG, and Total-C, and increases HDL-C. The magnitude of individual lipid and lipoprotein responses may be influenced by the severity and type of underlying lipid abnormality. The increase in HDL-C is associated with an increase in apolipoprotein A-I (Apo A-I) and a shift in the distribution of HDL subfractions. These shifts include an increase in the HDL2:HDL3 ratio, and an elevation in lipoprotein A-I (Lp A-I, an HDL-C particle containing only Apo A-I). Niacin treatment also decreases serum levels of apolipoprotein B-100 (Apo B), the major protein component of the very low-density lipoprotein (VLDL) and LDL fractions, and of Lp(a), a variant form of LDL independently associated with coronary risk. In addition, preliminary reports suggest that niacin causes favorable LDL particle size transformations, although the clinical relevance of this effect requires further investigation.

Simvastatin

Simvastatin reduces elevated total-C, LDL-C, Apo B, and TG, and increases HDL-C in patients with primary heterozygous familial and nonfamilial hypercholesterolemia and mixed dyslipidemia. Simvastatin reduces total-C and LDL-C in patients with homozygous familial hypercholesterolemia. Simvastatin decreases VLDL, total-C/HDL-C ratio, and LDL-C/HDL-C ratio.

12.3 Pharmacokinetics

Absorption and Bioavailability

SIMCOR

The relative bioavailability of niacin (Nicotinuric acid, NUA, Cmax and total urinary excretion as the surrogate), simvastatin, and simvastatin acid was evaluated under a light snack conditions in healthy volunteers (n=42), following administration of two 1000/20 mg SIMCOR tablets. Niacin exposure (Cmax and AUC) after SIMCOR was similar to that of a niacin extended-release formulation. However, simvastatin and simvastatin acid AUC after SIMCOR increased by 23% and 41%, respectively, compared to those of a simvastatin immediate release formulation. The mean time to Cmax (Tmax) for niacin ranged from 4.6 to 4.9 hours and simvastatin from 1.9 to 2.0 hours. Following administration of 2 x 1000/20 mg SIMCOR, the mean Cmax, Tmax and AUC(0-t) for simvastatin acid, active metabolite of simvastatin, were 3.29 ng/mL, 6.56 hours and 30.81 ng.hr/mL respectively.

Bioequivalence has not been evaluated among different SIMCOR dosage strengths except between 1000/40 and 500/20 mg. SIMCOR tablets 1000/40 mg and 500/20 mg were bioequivalent following a single dose of 2000/80 mg. Therefore, dosage strengths of SIMCOR should not be considered exchangeable except between these two strengths.

Niacin

Due to extensive and saturable first-pass metabolism, niacin concentrations in the general circulation are dose dependent and highly variable. Peak steady-state niacin concentrations were 0.6, 4.9, and 15.5 mcg/mL after doses of 1000, 1500, and 2000 mg NIASPAN once daily (given as two 500 mg, two 750 mg, and two 1000 mg tablets, respectively). To reduce the risk of gastrointestinal upset, administration of niacin extended-release with a low-fat meal or snack is recommended.

Simvastatin

Since simvastatin undergoes extensive first-pass extraction in the liver, the availability of the drug to the general circulation is low (<5%). Peak plasma concentrations of both active and total inhibitors were attained within 1.3 to 2.4 hours postdose. Following an oral dose of ^14C-labeled simvastatin in man, plasma concentration of total radioactivity (simvastatin plus ^14C-metabolites) peaked at 4 hours and declined rapidly to about 10% of peak by 12 hours postdose. Relative to the fasting state, the plasma profile of inhibitors was not affected when simvastatin was administered immediately before an American Heart Association recommended low-fat meal.

Metabolism

SIMCOR

Following administration of SIMCOR, niacin and simvastatin undergo rapid and extensive first-pass metabolism as described in the following niacin and simvastatin sections. Following administration of 2 x 1000/20 mg SIMCOR in healthy volunteers, 10.2%, 10.7%, and 29.5% of the administered niacin dose was recovered in urine as niacin metabolites, NUA, N-methylnicotinamide (MNA), and N-methyl-2-pyridone-5-carboxamide (2PY), respectively. Following administration of 2 x 1000/20 mg SIMCOR, the mean Cmax, Tmax, and AUC(0-t) for the simvastatin metabolite, simvastatin acid were 3.29 ng/mL, 6.56hours, and 30.81ng·hr/mL respectively.

Niacin

Niacin undergoes rapid and extensive first-pass metabolism that is dose-rate specific and, at the doses used to treat dyslipidemia, saturable. In humans, one pathway is through a simple conjugation step with glycine to form NUA. NUA is then excreted, although there may be a small amount of reversible metabolism back to niacin. The other pathway results in the formation of nicotinamide adenine dinucleotide (NAD). It is unclear whether nicotinamide is formed as a precursor to, or following the synthesis of, NAD. Nicotinamide is further metabolized to at least MNA and nicotinamide-N-oxide NNO. MNA is further metabolized to two other compounds, 2PY and N-methyl-4-pyridone-5-carboxamide (4PY). The formation of 2PY appears to predominate over 4PY in humans.

Simvastatin

Simvastatin is a substrate of CYP3A4. Simvastatin is a lactone that is readily hydrolyzed in vivo to the corresponding β-hydroxyacid, a potent inhibitor of HMG-CoA reductase. The major active metabolites of simvastatin present in human plasma are the β-hydroxyacid of simvastatin and its 6’-hydroxy, 6’-hydroxymethyl, and 6’-exomethylene derivatives.

Elimination

SIMCOR

Following 2 x 1000/20 mg SIMCOR administration, approximately 54% of the niacin dose administered was recovered in urine in 96 hours as niacin and metabolites of which 3.6% was recovered as niacin.

After SIMCOR administration, the mean terminal plasma half-life for simvastatin was 4.2 to 4.9 hours and for simvastatin acid was 4.6 to 5.0 hours.

Niacin

Niacin and its metabolites are rapidly eliminated in the urine. Following single and multiple doses of 1500 to 2000 mg niacin, approximately 53 to 77% of the niacin dose administered as NIASPAN was recovered in urine as niacin and metabolites; up to 7.7% of the dose was recovered in urine as unchanged niacin after multiple dosing with 2 x 1000 mg NIASPAN. The ratio of metabolites recovered in the urine was dependent on the dose administered.

Simvastatin

Simvastatin is excreted in urine, based on studies in humans. Following an oral dose of ^14C-labeled simvastatin in man, 13% of the dose was excreted in urine and 60% in feces.

Special Populations

A pharmacokinetic study with simvastatin showed the mean plasma level of HMG-CoA reductase inhibitory activity to be approximately 45% higher in elderly patients between 70-78 years of age compared with patients between 18-30 years of age.

Steady-state plasma concentrations of niacin and metabolites after administration of niacin extended-release are generally higher in women than in men, with the magnitude of the difference varying with dose and metabolite. Recovery of niacin and metabolites in urine, however, is generally similar for men and women, indicating that absorption is similar for both genders. The gender differences observed in plasma levels of niacin and its metabolites may be due to gender-specific differences in metabolic rate or volume of distribution.

Pharmacokinetic studies with a statin having a similar principal route of elimination to that of simvastatin have suggested that for a given dose level, higher systemic exposure may be achieved in patients with severe renal insufficiency (as measured by creatinine clearance).

13 NONCLINICAL TOXICOLOGY

13.1 Carcinogenesis, Mutagenesis, Impairment of Fertility

No studies have been conducted with SIMCOR regarding carcinogenesis, mutagenesis, or impairment of fertility.

Niacin

Niacin, administered to mice for a lifetime as a 1% solution in drinking water, was not carcinogenic. The mice in this study received approximately 6 to 8 times a human dose of 3000 mg/day as determined on a mg/m^2 basis. Niacin was negative for mutagenicity in the Ames test. No studies on impairment of fertility have been performed.

Simvastatin

In a 72-week carcinogenicity study, mice were administered daily doses of simvastatin of 25, 100, and 400 mg/kg body weight, which resulted in mean plasma drug levels approximately 1, 4, and 8 times higher than the mean human plasma drug level, respectively (as total inhibitory activity based on AUC) after an 80-mg oral dose. Liver carcinomas were significantly increased in high-dose females and mid- and high-dose males with a maximum incidence of 90% in males. The incidence of adenomas of the liver was significantly increased in mid- and high-dose females. Drug treatment also significantly increased the incidence of lung adenomas in mid- and high-dose males and females. Adenomas of the Harderian gland (a gland of the eye of rodents) were significantly higher in high-dose mice than in controls. No evidence of a tumorigenic effect was observed at 25 mg/kg/day.

In a separate 92-week carcinogenicity study in mice at doses up to 25 mg/kg/day, no evidence of a tumorigenic effect was observed (mean plasma drug levels were 1 times higher than humans given 80 mg simvastatin as measured by AUC). In a two-year study in rats at 25 mg/kg/day, there was a statistically significant increase in the incidence of thyroid follicular adenomas in female rats exposed to approximately 11 times higher levels of simvastatin than in humans given 80 mg simvastatin (as measured by AUC). A second two-year rat carcinogenicity study with doses of 50 and 100 mg/kg/day produced hepatocellular adenomas and carcinomas (in female rats at both doses and in males at 100 mg/kg/day). Thyroid follicular cell adenomas were increased in males and females at both doses; thyroid follicular cell carcinomas were increased in females at 100 mg/kg/day. The increased incidence of thyroid neoplasms appears to be consistent with findings from other HMG-CoA reductase inhibitors. These treatment levels represented plasma drug levels (AUC) of approximately 7 and 15 times (males) and 22 and 25 times (females) the mean human plasma drug exposure after an 80 milligram daily dose. No evidence of mutagenicity was observed in a microbial mutagenicity (Ames) test with or without rat or mouse liver metabolic activation. In addition, no evidence of damage to genetic material was noted in an in vitro alkaline elution assay using rat hepatocytes, a V-79 mammalian cell forward mutation study, an in vitro chromosome aberration study in CHO cells, or an in vivo chromosomal aberration assay in mouse bone marrow. There was decreased fertility in male rats treated with simvastatin for 34 weeks at 25 mg/kg body weight (4 times the maximum human exposure level, based on AUC, in patients receiving 80 mg/day); however, this effect was not observed during a subsequent fertility study in which simvastatin was administered at this same dose level to male rats for 11 weeks (the entire cycle of spermatogenesis including epididymal maturation). No microscopic changes were observed in the testes of rats from either study. At 180 mg/kg/day, (which produces exposure levels 22 times higher than those in humans taking 80 mg/day based on surface area, mg/m^2), seminiferous tubule degeneration (necrosis and loss of spermatogenic epithelium) was observed. In dogs, there was drug-related testicular atrophy, decreased spermatogenesis, spermatocytic degeneration and giant cell formation at 10 mg/kg/day, (approximately 2 times the human exposure, based on AUC, at 80 mg/day). The clinical significance of these findings is unclear.

13.2 Animal Toxicology and/or Pharmacology

SIMCOR

No animal toxicology or pharmacology studies were done with SIMCOR.

Niacin

No animal toxicology or pharmacology studies were done with niacin extended-release.

Simvastatin

Optic nerve degeneration was seen in clinically normal dogs treated with simvastatin for 14 weeks at 180 mg/kg/day, a dose that produced mean plasma drug levels about 12 times higher than the mean plasma drug level in humans taking 80 mg/day. A chemically similar drug in this class also produced optic nerve degeneration (Wallerian degeneration of retinogeniculate fibers) in clinically normal dogs in a dose-dependent fashion starting at 60 mg/kg/day, a dose that produced mean plasma drug levels about 30 times higher than the mean plasma drug level in humans taking the highest recommended dose (as measured by total enzyme inhibitory activity). This same drug also produced vestibulocochlear Wallerian-like degeneration and retinal ganglion cell chromatolysis in dogs treated for 14 weeks at 180 mg/kg/day, a dose that resulted in a mean plasma drug level similar to that seen with the 60 mg/kg/day dose.

Central Nervous System (CNS) vascular lesions, characterized by perivascular hemorrhage and edema, mononuclear cell infiltration of perivascular spaces, perivascular fibrin deposits and necrosis of small vessels were seen in dogs treated with simvastatin at a dose of 360 mg/kg/day, a dose that produced mean plasma drug levels that were about 14 times higher than the mean plasma drug levels in humans taking 80 mg/day. Similar CNS vascular lesions have been observed with several other drugs of this class.

There were cataracts in female rats after two years of simvastatin treatment with 50 and 100 mg/kg/day (22 and 25 times the human AUC at 80 mg/day, respectively) and in dogs after three months at 90 mg/kg/day (19 times) and at two years at 50 mg/kg/day (5 times).

Reproductive Toxicology Studies

Simvastatin was not teratogenic in rats at doses of 25 mg/kg/day or in rabbits at doses up to 10 mg/kg/day. These doses resulted in 3 times (rat) or 3 times (rabbit) the human exposure based on mg/m^2 surface area. However, in studies with another structurally-related HMG-CoA reductase inhibitor, skeletal malformations were observed in rats and mice.

14 CLINICAL STUDIES

14.1 Modifications of Lipid Profiles

SIMCOR

In a double-blind, randomized, multicenter, multi-national, active-controlled, 24-week study, the lipid effects of SIMCOR were compared to simvastatin 20 mg and 80 mg in 641 patients with type II hyperlipidemia or mixed dyslipidemia. Following a lipid qualification phase, patients were eligible to enter one of two treatment groups. In Group A, patients on simvastatin 20 mg monotherapy with elevated non-HDL levels and LDL-C levels at goal, per the NCEP guidelines, were randomized to one of three treatment arms: SIMCOR 1000/20 mg, SIMCOR 2000/20 mg, or simvastatin 20 mg. In Group B, patients on simvastatin 40 mg monotherapy, with elevated non-HDL levels per the NCEP guidelines regardless of attainment of LDL-C goals, were randomized to one of three treatment arms: SIMCOR 1000/40 mg, SIMCOR 2000/40 mg, or simvastatin 80 mg. Therapy was initiated at the 500 mg dose of SIMCOR and increased by 500 mg every four weeks. Thus patients were titrated to the 1000 mg dose of SIMCOR after four weeks and to the 2000 mg dose of SIMCOR after 12 weeks. All patients randomized to simvastatin monotherapy received 50 mg immediate-release niacin daily in an attempt to keep the study from becoming unblinded due to flushing in the SIMCOR groups. Patients were instructed to take one 325 mg aspirin 30 minutes prior to taking the double-blind medication to help minimize flushing effects.

In Group A, the primary efficacy analysis was a comparison of the mean percent change in non-HDL levels between the SIMCOR 2000/20 mg and simvastatin 20 mg groups, and if statistically significant, then a comparison was conducted between the SIMCOR 1000/20 mg and simvastatin 20 mg groups. In Group B, the primary efficacy analysis was a determination of whether the mean percent change in non-HDL in the SIMCOR 2000/40 mg group was non-inferior to the mean percent change in the simvastatin 80 mg group, and if so, whether the mean percent change in non-HDL in the SIMCOR 1000/40 mg group was non-inferior to the mean percent change in the simvastatin 80 mg group.

In Group A, the non-HDL-C lowering with SIMCOR 2000/20 and SIMCOR 1000/20 was statistically significantly greater than that achieved with simvastatin 20 mg after 24 weeks (p<0.05; Table 4). The completion rate after 24 weeks was 72% for the SIMCOR arms and 88% for the simvastatin 20 mg arm. In Group B, the non-HDL-C lowering with SIMCOR 2000/40 and SIMCOR 1000/40 was non-inferior to that achieved with simvastatin 80 mg after 24 weeks (Table 5). The completion rate after 24 weeks was 78% for the SIMCOR arms and 80% for the simvastatin 80 mg arm.

SIMCOR was not superior to simvastatin in lowering LDL-C in either Group A or Group B. However, SIMCOR was superior to simvastatin in both groups in lowering TG and raising HDL (Tables 6 and 7).

Table 4. Non-HDL Treatment Response Following 24-Week Treatment Mean Percent Change from Simvastatin 20-mg Treated Baseline
Group A
 | SIMCOR 2000/20 |  |  | SIMCOR 1000/20 |  |  | Simvastatin 20
Week | na | dose (mg/mg) | non-HDLb | na | Dose (mg/mg) | non-HDLb | na | Dose (mg/mg) | non-HDLb
Baseline | 56 | --- | 163.1 mg/dL | 108 | --- | 164.8 mg/dL | 102 | --- | 163.7 mg/dL
4 | 52 | 500/20 | -12.9% | 86 | 500/20 | -12.8% | 91 | 20 | -8.3%
8 | 46 | 1000/20 | -17.5% | 91 | 1000/20 | -15.5% | 95 | 20 | -8.3%
12 | 46 | 1500/20 | -18.9% | 90 | 1000/20 | -14.8% | 96 | 20 | -6.4%
24 | 40 | 2000/20 | -19.5%† | 78 | 1000/20 | -13.6%† | 90 | 20 | -5.0%
Dropouts by week 24: | 28.6% |  |  | 27.8% |  |  | 11.8%
a n=number of subjects with values in the analysis window at each timepoint
b The percent change from baseline is the model-based mean from a repeated measures mixed model with no imputation for missing data from study dropouts.
† significant vs. simvastatin 20 mg at the primary endpoint (Week 24), p<0.05

Table 5. Non-HDL Treatment Response Following 24-Week Treatment Mean Percent Change from Simvastatin 40-mg Treated Baseline
Group B
 | SIMCOR 2000/40 |  |  | SIMCOR 1000/40 |  |  | Simvastatin 80
Week | na | dose (mg/mg) | non-HDLb | na | Dose (mg/mg) | non-HDLb | na | Dose (mg/mg) | non-HDLb
Baseline | 98 | --- | 144.4 mg/dL | 111 | --- | 141.2 mg/dL | 113 | --- | 134.5 mg/dL
4 | 96 | 500/40 | -6.0% | 108 | 500/40 | -5.9% | 110 | 80 | -11.3%
8 | 93 | 1000/40 | -15.5% | 100 | 1000/40 | -16.2% | 104 | 80 | -13.7%
12 | 90 | 1500/40 | -18.4% | 97 | 1000/40 | -12.6% | 100 | 80 | -9.5%
24 | 80 | 2000/40 | -7.6%c | 82 | 1000/40 | -6.7%d | 90 | 80 | -6.0%
Dropouts by week 24: | 18.4% |  |  | 26.1% |  |  | 20.4%
a n=number of subjects with values in the analysis window at each timepoint
b The percent change from baseline is the model-based mean from a repeated measures mixed model with no imputation for missing data from study dropouts.
c non-inferior to Simvastatin 80 arm; 95% confidence interval of mean difference in non-HDL for SIMCOR 2000/40 vs. Simvastatin 80 is (-7.7%, 4.5%)
d non-inferior to Simvastatin 80 arm; 95% confidence interval of mean difference in non-HDL for SIMCOR 1000/40 vs. SIMCOR 80 is (-6.6%, 5.3%)

Table 6. Mean Percent Change from Baseline to Week 24 in Lipoprotein Lipid Levels
Treatment Group A
TREATMENT | N | LDL-C | Total-C | HDL-C | TGa | Apo B
Baseline (mg/dL)* | 266 | 120 | 207 | 43 | 209 | 102
Simvastatin 20 mg | 102 | -6.7% | -4.5% | 7.8% | -15.3% | -5.6%
SIMCOR 1000/20 | 108 | -11.9% | -8.8% | 20.7% | -26.5% | -13.2%
SIMCOR 2000/20 | 56 | -14.3% | -11.1% | 29.0% | -38.0% | -18.5%
* either treatment naïve or after receiving simvastatin 20 mg
a medians are reported for TG

Table 7. Mean Percent Change from Baseline to Week 24 in Lipoprotein Lipid Levels
Treatment Group B
TREATMENT | N | LDL-C | Total-C | HDL-C | TGa | Apo B
Baseline (mg/dL)* | 322 | 108 | 187 | 47 | 145 | 93
Simvastatin 80 mg | 113 | -11.4% | -6.2% | 0.1% | 0.3% | -7.5%
SIMCOR 1000/40 | 111 | -7.1% | -3.1% | 15.4% | -22.8% | -7.7%
SIMCOR 2000/40 | 98 | -5.1% | -1.6% | 24.4% | -31.8% | -10.5%
* after receiving simvastatin 40 mg
a medians are reported for TG

Limitations of use

No incremental benefit of SIMCOR on cardiovascular morbidity and mortality over and above that demonstrated for simvastatin monotherapy and niacin monotherapy has been established.

16 HOW SUPPLIED/STORAGE AND HANDLING

SIMCOR 500 mg/20 mg, 750 mg/20 mg and 1000 mg/20 mg tablets are available as blue, unscored, tablets, printed with black ink.

SIMCOR 1000 mg/40 mg tablets are available as dark blue, unscored, tablets, printed with white ink.

Each tablet is printed on one side with the Abbott “A” and a code number specific to the tablet strength. Please see the table below:

SIMCOR Tablet Strength | Printed ID | NDC Number | Packaged in
500 mg/20 mg | A 500-20 | 54868-5886-0 | Bottles of 30
500 mg/20 mg | A 500-20 | 54868-5886-1 | Bottles of 60
750 mg/20 mg | A 750-20 | 54868-5907-0 | Bottles of 30
750 mg/20 mg | A 750-20 | 54868-5907-1 | Bottles of 60
1000 mg/20 mg | A 1000-20 | 54868-5904-0 | Bottles of 30
1000 mg/20 mg | A 1000-20 | 54868-5904-1 | Bottles of 60
1000 mg/40 mg | A 1000-40 | 54868-6169-0 | Bottles of 30

Storage: Store at controlled room temperature 20º-25ºC (68º-77ºF).

17 PATIENT COUNSELING INFORMATION

The patient should be informed of the following:

17.1 Dosing Time

SIMCOR tablets should be taken at bedtime, after a low-fat snack. Administration on an empty stomach is not recommended.

17.2 Tablet Integrity

SIMCOR tablets should not be broken, crushed or chewed, but should be swallowed whole.

17.3 Dosing Interruption

If dosing is interrupted for any length of time, their physician should be contacted prior to re-starting therapy; re-titration is recommended.

17.4 Muscle Pain

To notify their physician of any unexplained muscle pain, tenderness, or weakness promptly. The risk of this occurring is increased when taking certain types of medication or consuming larger quantities of grapefruit juice. They should discuss all medication, both prescription and over the counter, with their physician.

17.5 Flushing

Flushing is a common side effect of niacin therapy that may subside after several weeks of consistent SIMCOR use. Flushing may vary in severity and is more likely to occur with initiation of therapy, or during dose increases. By dosing at bedtime, flushing will most likely occur during sleep. However, if awakened by flushing at night, the patient should get up slowly, especially if feeling dizzy, feeling faint, or taking blood pressure medications.

17.6 Use of Aspirin

Taking aspirin approximately 30 minutes before dosing can minimize flushing.

17.7 Diet

To avoid ingestion of alcohol, hot beverages and spicy foods around the time of taking SIMCOR to minimize flushing.

17.8 Supplements

To notify their physician if they are taking vitamins or other nutritional supplements containing niacin or nicotinamide.

17.9 Dizziness

To notify their physician if symptoms of dizziness occur.

17.10 Diabetics

If diabetic, to notify their physician of changes in blood glucose.

17.11 Pregnancy

Women of childbearing age should use an effective method of birth control to prevent pregnancy while using SIMCOR. Discuss future pregnancy plans with your healthcare professional, and discuss when to stop SIMCOR if you are trying to conceive. If you are pregnant, stop SIMCOR and call your healthcare professional.

17.12 Breastfeeding

Women who are breastfeeding should not use SIMCOR. If you have a lipid disorder and are breastfeeding, speak with your healthcare professionals about your lipid disorder and whether or not you should breastfeed your infant.

Manufactured by Abbott Pharmaceuticals PR Ltd., Barceloneta, PR 00617

for Abbott Laboratories North Chicago, IL 60064, U.S.A.

Relabeling and Repackaging by: Physicians Total Care, Inc., Tulsa, OK 74146

PRINCIPAL DISPLAY PANEL - 500 mg/20 mg

Simcor® Niacin Extended-Release/ Simvastatin Tablets 500 mg/20 mg

PRINCIPAL DISPLAY PANEL 750 mg/20 mg

Simcor® Niacin Extended-Release/ Simvastatin Tablets 750 mg/20 mg

PRINCIPAL DISPLAY PANEL - 1000 mg/20 mg

Simcor® Niacin Extended-Release/ Simvastatin Tablets 1000 mg/20 mg

Simcor® Niacin Extended-Release/ Simvastatin Tablets 1000 mg/40 mg